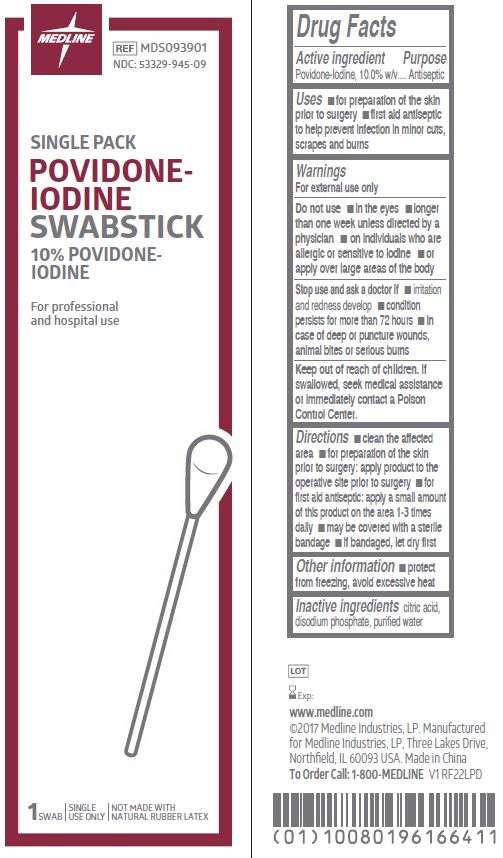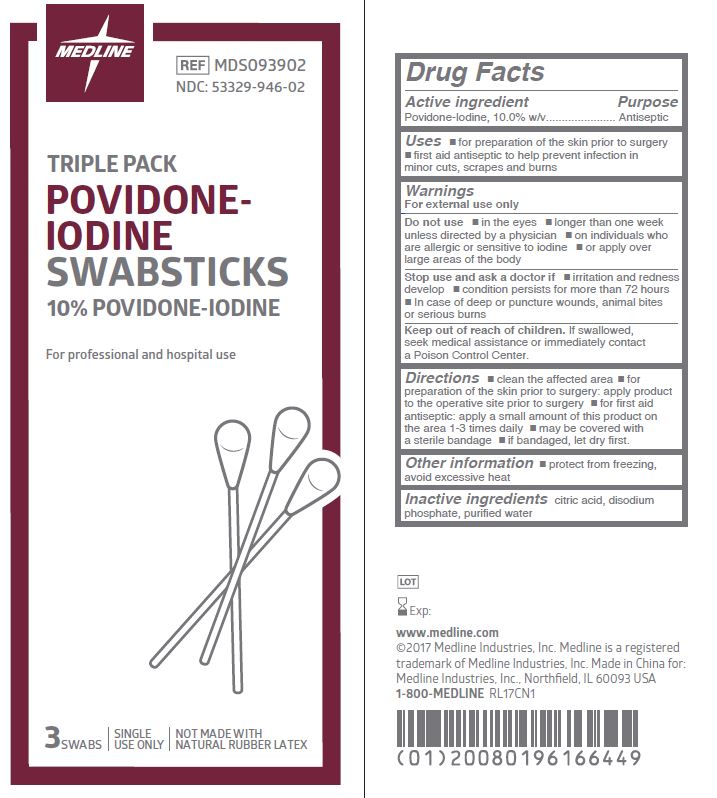 DRUG LABEL: Povidone-Iodine
NDC: 53329-945 | Form: SWAB
Manufacturer: Medline Industries, LP
Category: otc | Type: HUMAN OTC DRUG LABEL
Date: 20251023

ACTIVE INGREDIENTS: POVIDONE-IODINE 10 mg/1 mL
INACTIVE INGREDIENTS: CITRIC ACID MONOHYDRATE; WATER; SODIUM PHOSPHATE, DIBASIC, ANHYDROUS

945/946 Medline PVP Swabs

Active ingredient

Povidone-Iodine, 10.0% w/v

Purpose

Antiseptic

Uses

- for preparation of the skin prior to surgery
- first aid antiseptic to help prevent infection in minor cuts, scrapes and burns

Warnings

For external use only

Do not use

- in the eyes
- longer than one week unless directed by a physician
- on individuals who are allergic or sensitive to iodine
- or apply over large areas of the body

Stop use and ask a doctor

- irritation and redness develop
- condition persists for more than 72 hours
- In case of deep or puncture wounds, animal bites or serious burns

Keep out of reach of children.

If swallowed, seek medical assistance or immediately contact a Poison Control Center.

Directions

- Clean the affected area.
- For preparation of the skin prior to surgery: apply product to the operative site prior to surgery
- For first aid antiseptic: apply a small amount of this product on the area 1-3 times daily. May be covered with a sterile bandage. If bandaged, let dry first.

Other information

- protect from freezing, avoid excessive heat

Inactive ingredients

citric acid, disodium phosphate, purified water

Manufacturing Information

www.medline.com

©2017 Medline Industries, LP.

Manufactured for
Medline Industries, LP
Three Lakes Drive, Northfield, IL 60093 USA
Made in China
1-800-MEDLINE

REF: MDS093901